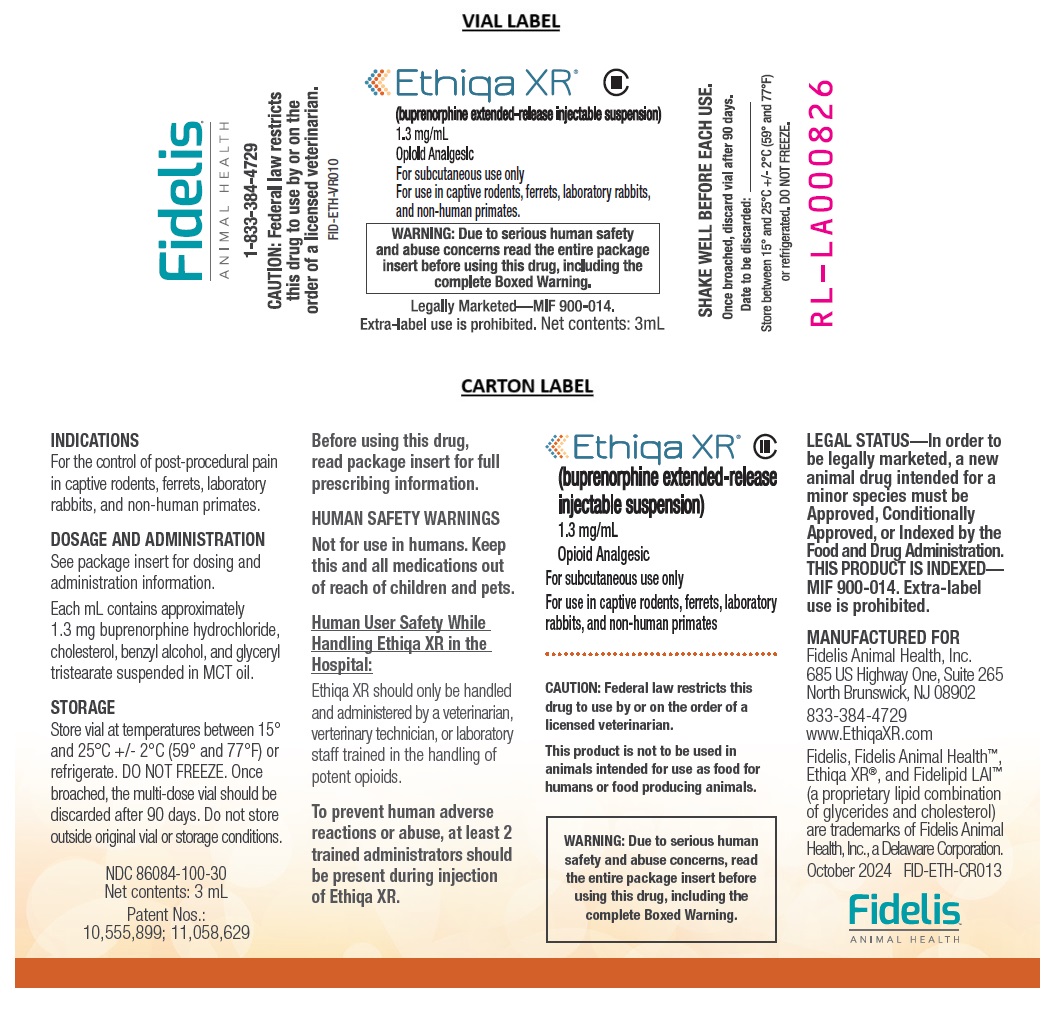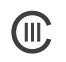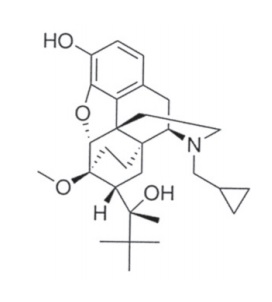 DRUG LABEL: Ethiqa XR
NDC: 86084-100 | Form: INJECTION, SUSPENSION, EXTENDED RELEASE
Manufacturer: Fidelis Animal Health, Inc.
Category: animal | Type: PRESCRIPTION ANIMAL DRUG LABEL
Date: 20251006
DEA Schedule: CIII

ACTIVE INGREDIENTS: BUPRENORPHINE HYDROCHLORIDE 1.3 mg/1 mL
INACTIVE INGREDIENTS: CHOLESTEROL; BENZYL ALCOHOL; GLYCERYL TRISTEARATE; MEDIUM-CHAIN TRIGLYCERIDES

Ethiqa XR® (buprenorphine extended-release injectable suspension)

Ethiqa XR®
(buprenorphine extended-release injectable suspension)
1.3 mg/mL
Opioid Analgesic
For subcutaneous use only
For use in captive rodents, ferrets, laboratory rabbits, and non-human primates.

CAUTION: Federal law restricts this drug to use by or on the order of a licensed veterinarian.

LEGAL STATUS--In order to be legally marketed, a new animal drug intended for a minor species must be Approved, Conditionally Approved, or Indexed by the Food and Drug Administration. THIS PRODUCT IS INDEXED--MIF 900-014. Extra-label use is prohibited.

This product is not to be used in animals intended for use as food for humans or food-producing animals.

ABUSE

HUMAN SAFETY WARNING

Abuse Potential
ETHIQA XR contains buprenorphine, an opioid that exposes humans to risks of misuse, abuse, and addiction, which can lead to overdose and death. Use of buprenorphine may lead to physical dependence. The risk of abuse by humans should be considered when storing, administering, and disposing of ETHIQA XR. Persons at increased risk for opioid abuse include those with a personal or family history of substance abuse (including drugs or alcohol) or mental illness (e.g., depression).

Life-Threatening Respiratory Depression
Serious, life-threatening, or fatal respiratory depression may occur with accidental exposure to or with misuse or abuse of ETHIQA XR. Monitor for respiratory depression if human exposure to buprenorphine occurs. Misuse or abuse of buprenorphine by swallowing, snorting, or injecting poses a significant risk of overdose and death.

Accidental Exposure
Because of the potential for adverse reactions associated with accidental exposure, ETHIQA XR should only be administered by veterinarians, veterinary technicians, or laboratory staff who are trained in the handling of potent opioids. Accidental exposure to ETHIQA XR, especially in children, can result in a fatal overdose of buprenorphine.

Risks From Concurrent Misuse or Abuse with Benzodiazepines or Other CNS Depressants

Concurrent misuse or abuse of opioids with benzodiazepines or other central nervous system (CNS) depressants, including alcohol, may result in profound sedation, respiratory depression, coma, and death.

See HUMAN SAFETY WARNINGS for detailed information.

DESCRIPTION

Ethiqa XR is an injectable suspension of extended-release buprenorphine. Ethiqa XR is an extended-release formulation using the Fidelipid LAI™ technology, a proprietary lipid combination of glycerides and cholesterol. Buprenorphine hydrochloride, an opioid analgesic, is the active ingredient in Ethiqa XR. Lipid-bound buprenorphine hydrochloride is suspended in medium chain fatty acid triglyceride (MCT) oil. Lipids encapsulate the buprenorphine limiting diffusion which provides for larger doses and prolonged action. ^1,2 Ethiqa XR has a slightly yellow to white opaque appearance. Each mL contains approximately 1.3 mg buprenorphine hydrochloride. The sterile product contains cholesterol, benzyl alcohol, glyceryl tristearate, and buprenorphine hydrochloride suspended in MCT oil. Buprenorphine belongs to the opioid class of drugs and is a narcotic under the Controlled Substances Act due to its chemical derivation from thebaine.

Buprenorphine

Formula C29H41NO4

INDICATIONS

Ethiqa XR is indicated for the control of post-procedural pain in captive rodents, ferrets, laboratory rabbits, and non-human primates.

DOSAGE AND ADMINISTRATION

Wear protective clothing when administering Ethiqa XR.

Do not dispense Ethiqa XR for administration at home by the pet owner (see HUMAN SAFETY WARNINGS).

Dosing

Administer Ethiqa XR subcutaneously according to the dose listed in the table for the appropriate species.

Doses were derived either from published literature or using allometric principles.

Consider the time to reach estimated therapeutic blood levels when administering Ethiqa XR for post-procedural pain. If needed, a single repeat dose may be administered subcutaneously 72 hours after the initial dose.

Definitive therapeutic blood levels of Ethiqa XR have not been established for all species. The times to reach blood levels thought to be therapeutic is presented below and is representative of what has been found in published literature.

For more information, consult the published literature referenced at the end of this package insert.

DOSING TABLE FOR SUBCUTANEOUS INJECTION OF ETHIQA XR

Species | Ethiqa XR Dose (mg/kg body weight) | Time to reach estimated therapeutic blood levels | Precautions/ Adverse Events
Mice | 3.25 mg/kg^10 | 30 minutes^10 | • Death has been reported when non-steroidal anti-inflammatory drugs (NSAIDs such as meloxicam and carprofen) and Ethiqa XR have been administered concomitantly.^5; • Granulomatous inflammatory nodules have been observed in naked-skinned mice and rats administered Ethiqa XR.^4,5; • In one study, two male mice died following the third surgery and redosing; weight loss.^11
Naked mole rats (NMR) | 3.25 mg/kg* |  | • No published data available administering Ethiqa XR to naked mole rats.
Gerbils | 1 mg/kg^13 | 30 minutes^13 | • Granulomatous inflammation at injection site.^13
Hamsters | 0.8 mg/kg* |  | • No published data available administering Ethiqa XR to hamsters.
Rats | 0.65 mg/kg^12 | 4 hours^16 | • Nausea within 24 hrs of dosing, self-licking, self-gnawing and efforts to eat wood-chip bedding, one out of 36 rats exposed to wood bedding died^3,12, 3 of 222 rats bled profusely from jugular vein, which was used for obtaining blood samples, and died.; • Granulomatous inflammatory nodules have been observed in naked-skinned mice and rats administered Ethiqa XR.^4,5
Chinchillas | 0.48 mg/kg* |  | • No published data available administering Ethiqa XR to chinchillas.
Guinea pigs | 0.48 mg/kg17* | 8 hours^17 | • Decrease in body weight^14,17and fecal output.^14 Increase in passive behavior, such as eyes closed or squinting, subtle body movement, and incomplete movement.^17
Prairie dogs | 0.48 mg/kg* |  | • No published data available administering Ethiqa XR to prairie dogs.
Ferrets | 0.6 mg/kg^9 | 30 minutes^9 | • No adverse reactions observed.^9
Non-human primates | 0.2 mg/kg^6 | 15 minutes^6 | • Injection site reactions including inflammation and necrosis have been observed in common marmosets.^6; • Mild sedation, decreased body weight, increased cage movements, acute necrosis and inflammation at the injection site.^6
Laboratory rabbits | 0.15 mg/kg^19 | • 60 minutes^19; • 30 minutes in female and 60 minutes in male rabbits^20 | • Reduced fecal output post-operatively. Returned to normal at 72 hours.^19

*These doses are based on allometric principles.

Allometric principles (i.e., animals among closely related species and of similar body size should have similar metabolic rates) can be used to determine the dose of Ethiqa XR for rodent species not listed in the table above and where no published data is available.

For example, doses for hamsters and guinea pigs were calculated using published allometric scaling factors (see Nair^21 and FDA^22 for detailed discussion and how to apply allometric scaling).

The dose of Ethiqa XR can also be estimated by using the known dose for a rodent species of similar size (the doses listed in the table above for NMR, chinchillas, and prairie dogs were calculated using this approach).

Based upon the time to reach estimated therapeutic blood levels, Ethiqa XR can be administered 30 minutes prior to painful stimulus in mice^10 and gerbils^13, 8-12 hours prior in guinea pigs^17, 60 minutes prior in laboratory rabbits^19, and 15 minutes prior in non-human primates.^6

Administration

Shake the vial well before each use to ensure uniform suspension. If stored refrigerated, bring to room temperature before use.

Use aseptic technique to subcutaneously administer Ethiqa XR by utilizing minimally stressful restraint techniques or sedation.

An oily sheen may be observed in the fur after injection due to leakage of Ethiqa XR, which is an oil-based drug suspension, from the injection site. The oily sheen may last for 4 to 5 days post-injection. Leakage from the injection site can be minimized by slowly injecting Ethiqa XR into the subcutaneous space.

Do not return any unused drug suspension from the syringe back into the vial.

The animal can be returned to its cage immediately after receiving Ethiqa XR. (See CONTRAINDICATIONS, PRECAUTIONS, and DOSAGE AND ADMINISTRATION for additional information on bedding.)

CONTRAINDICATIONS

Only administer Ethiqa XR by subcutaneous injection. Ethiqa XR is not intended for intravenous, intra-arterial, intrathecal, intramuscular, or intra-peritoneal injection.

Do not use in animals with pre-existing respiratory compromise.

Do not house rats on wood chip-type bedding after administration of Ethiqa XR. Signs of nausea, including pica, have been observed in rats for up to 3 days post-treatment with Ethiqa XR. Pica involving wood chip type bedding can be lethal (see ADVERSE REACTIONS).

HUMAN SAFETY WARNINGS

Not for use in humans. Keep this and all medications out of reach of children and pets.

Human User Safety While Handling Ethiqa XR in the Hospital:
Ethiqa XR should only be handled and administered by a veterinarian, veterinary technician, or laboratory staff trained in the handling of potent opioids.

To prevent human adverse reactions or abuse, at least 2 trained administrators should be present during injection of Ethiqa XR.

Wear protective clothing when administering Ethiqa XR.

Mucous Membrane or Eye Contact During Application:
Direct contact of Ethiqa XR with the eyes, oral, or other mucous membranes could result in absorption of buprenorphine and the potential for adverse reactions. If accidental eye, oral, or other mucous membrane contact is made during application, flush the area with water and contact a physician immediately. If wearing contact lenses, flush the eye first and then remove the contact lens.

Skin Contact During Application:
If human skin is accidentally exposed to ETHIQA XR, wash the exposed area immediately with soap and water and contact a physician. Accidental exposure could result in absorption of buprenorphine and the potential for adverse reactions.

Drug Abuse, Addiction, and Diversion of Opioids:
Controlled Substance:
Ethiqa XR contains buprenorphine, a Schedule III controlled substance with an abuse potential similar to other Schedule III opioids.

Abuse:
Ethiqa XR contains buprenorphine, an opioid substance, that can be abused and is subject to misuse, abuse, and addiction, which may lead to overdose and death. This risk is increased with concurrent use of alcohol and other central nervous system depressants, including other opioids and benzodiazepines.

Ethiqa XR should be handled appropriately to minimize the risk of diversion, including restriction of access, the use of accounting procedures, and proper disposal methods, as appropriate to the clinical setting and as required by law.

Prescription drug abuse is the intentional, non-therapeutic use of a prescription drug, even once, for its rewarding psychological or physiological effects. Buprenorphine has been diverted for non-medical use into illicit channels of distribution. All people handling opioids require careful monitoring for signs of abuse.

Storage and Disposal:
Ethiqa XR is a Schedule III opioid. Store in a locked cabinet according to federal and state controlled substance requirements/guidelines. Discard any broached vials after 90 days. Any unused or expired vials must be destroyed by a reverse distributor; for further information, contact your local DEA field office or call Fidelis Animal Health at 1-833-384-4729.

Information for Physician:
Ethiqa XR contains a mu opioid partial agonist (1.3 mg buprenorphine/mL). In the case of an emergency, provide the physician with this package insert. Naloxone may not be effective in reversing respiratory depression produced by buprenorphine. The onset of naloxone effect may be delayed by 30 minutes or more. Doxapram hydrochloride has also been used as a respiratory stimulant.

PRECAUTIONS

The use of paper or soft bedding for up to 3 days following administration of Ethiqa XR should be considered (see CONTRAINDICATIONS and ADVERSE REACTIONS).

Buprenorphine is excreted in the feces (see CLINICAL PHARMACOLOGY). Coprophagy may lead to ingestion of buprenorphine or its metabolites by animals treated with Ethiqa XR and untreated cage mates.

Ethiqa XR forms a depot near the injection site.

Animals may exhibit an obtunded response to stimuli up to 4 hours after receiving Ethiqa XR.

When using Ethiqa XR, an opiate antagonist such as naloxone, should be available in case reversal is required.

Ethiqa XR may cause sedation, decreased blood pressure, decreased heart rate, decreased gastrointestinal mobility, and respiratory depression. Use caution with concomitant administration of Ethiqa XR with drugs that cause respiratory depression.

Animals should be monitored for signs of decreased cardiovascular and respiratory function when receiving Ethiqa XR.

The safety of Ethiqa XR has not been evaluated in pregnant, lactating, neonatal, or immune-compromised animals.

Species-specific precautions described in the published literature are included in the dosing table under the DOSAGE AND ADMINISTRATION section.

ADVERSE REACTIONS

See the dosing table under the DOSAGE AND ADMINISTRATION section for species-specific adverse reactions.

CONTACT INFORMATION

Contact Fidelis Animal Health at 1-833-384-4729 or www.ethiqaxr.com. To report suspected adverse drug experiences, contact Fidelis Animal Health at 1-833-384-4729.

For additional information about reporting adverse drug experiences for animal drugs, contact FDA at 1-888-FDA-VETS or http://www.fda.gov/reportanimalae.

CLINICAL PHARMACOLOGY^3

Mechanism of Action: Buprenorphine exerts its analgesic effect via high affinity binding to various subclasses of opiate receptors particularly mu, in the central nervous system. Buprenorphine analgesic and adverse reactions are mediated by mu opioid receptor agonism. Due to its partial agonist activity, buprenorphine exhibits a ceiling effect to its actions and thus has a greater therapeutic index compared to full mu opioid receptor agonists such as morphine. Buprenorphine binds tightly to and dissociates slowly from the opioid receptor. Therefore, the pharmacological effects of buprenorphine are not directly related to plasma concentrations.

Buprenorphine can act as an agonist and antagonist at different classes of opioid receptors. Agonism at the mu opioid receptor and, in some cases, antagonism at the kappa or delta opioid receptors are possible underlying mechanisms for the ceiling effect and bell-shaped dose-response curve of buprenorphine. Studies with knockout mice have shown that the antinociceptive effect of buprenorphine, which is mediated primarily by the mu opioid receptor, is attenuated by the ability of the drug to activate the opioid receptor like (ORL-1) receptor. The drug can be described as a ‘full’ and a ‘partial’ agonist at the same receptor depending on the specific assay. There appears to be no ceiling effect for analgesia, but there is a ceiling effect for respiratory depression.

Pharmacokinetic studies with bolus injections of buprenorphine in mice and rats provide similar models. After bolus intravenous administration, plasma levels decline tri-exponentially. The drug is n-dealkylated in the liver to norbuprenorphine (NBN), an active metabolite. Studies have shown that glucuronide metabolites of buprenorphine and NBN are also metabolically active, and can approximate or exceed the concentration of the parent drug. Un-metabolized drug excreted in the urine and feces one week after injection was 1.9 and 22.4% of the dose, respectively, and 92% of the dose was accounted for in one week.^3

See the dosing table under DOSAGE AND ADMINISTRATION section for information specific to each species regarding time to reach estimated therapeutic blood levels.

HOW SUPPLIED

Ethiqa XR is supplied in a 5 mL glass vial containing 3 mL of injectable drug suspension.

STORAGE INFORMATION

Store between 15° and 25° C +/- 2°C (59° and 77°F) or refrigerated. DO NOT FREEZE. If stored refrigerated, bring to room temperature before use. Once broached, the multi-dose vial should be discarded after 90 days.

Product could change its physical properties if not stored within the specified storage conditions and original vial container.

REFERENCES

1. Mishra et al. Engineering solid lipid nanaparticles for improved drug delivery: promises and challenges of translational research. Drug Deliv. and Transl. Res, 2: 238-253; 2012.

2. Bethune et al., The role of drug-lipid interactions on the disposition of liposome-formulated opioid analgesics in vitro and in vivo. Anesth Analg. 93(4):928-33; 2001.

3. Guarnieri et al.,Safety and efficacy of buprenorphine for analgesia in laboratory mice and rats. Lab Animal, 41(11): 337-343; 2012.

4. Levinson BL, Leary SL, Bassett BJ, Cook CJ, GormanGS, Coward LU. Pharmacokinetic and Histopathologic Study of an Extended-Release, Injectable formulation of Buprenorphine in Sprague-Dawley Rats. J Am Assoc Lab Anim Sci. Jan 1, 61(1): 81-8; 2022.

5. Fidelis’ postmarketing surveillance database.

6. Fabian NJ et al. Evaluation and comparison of pharmacokinetic profiles and safety of two extended-release buprenorphine formulations in common marmosets (Callithrix jacchus). Scientific Reports, 13, 11864; 2023.

7. Klein H. et al. A pharmacokinetic study of extended-release buprenorphine in Cynomolgus monkeys (m.fascicularis). Journal of Medical Primatology. 52(6):369-373; 2023.

8. Williams W et al. Pharmacokinetics of sustained-release buprenorphine in adult baboons (Papio Anubis). 2021 National Meeting of the Am Assoc for Lab Anim Sci (virtual).

9. Katzenbach JE, Wittenburg LA, Allweiler SI, Gustafson DL, Johnson MS. Pharmacokinetics of single-dose buprenorphine, butorphanol, and hydromorphone in the domestic ferret (Mustela putorius furo). J Exotic Pet Med 27:95-102; 2018.

10. Chan G et al. Assessment of the Safety and Efficacy of Pre-emptive Use of Extended-release Buprenorphine for Mouse Laparotomy. J Am Assoc Lab Anim Sci 99(99): 1-7;2022.

11. Traul KA et al. Safety studies of post-surgical buprenorphine therapy for mice. Lab Anim. 49(2):100-110;2015.

12. Cowan A et al. Lack of adverse effects during a target animal safety trial of extended-release buprenorphine in Fisher 344 rats. Nature America, Inc. Jan Vol 45(1):28-34; 2016.

13. Bowie AR et al. Pharmacokinetics of Extended-release Buprenorphine in Mongolian Gerbils (Meriones unguiculatus). J Am Assoc Lab Anim Sci: 62 (6): 538-544; 2023.

14. Zanetti AS et al. Pharmacokinetics and adverse effects of 3 sustained-release buprenorphine dosages in healthy guinea pigs. J Am Assoc Lab Anim Sci 56 (6): 768-778; 2017.

15. Fox L et al. Analgesic Efficacy and Safety of Buprenorphine in Chinchillas (Chinchilla lanigera). J Am Assoc Lab Anim Sci 57 (3): 286-290; 2018.

16. Alamaw ED et al. Extended-release Buprenorphine, an FDA indexed Analgesic, Attenuates Mechanical Hypersensitivity in Rats (Rattus norvegicus). J Am Assoc Lab Anim Sci. 61 (1): 81-88; 2022.

17. Oliver VL et al. Evaluation of pain assessment techniques and analgesic efficacy in a female guinea pig model of surgical pain. Am Assoc Lab Anim Med. 56 (4): 425-435; 2017.

18: Hutson CL et al. Analgesia during Monkeypox Virus Experimental Challenge Studies in Prairie Dogs (Cynomys ludovicianus). J Am Assoc Lab Anim Sci. 58 (4):485-500; 2019.

19. Farkas MR, Dorn S, Muller L, et al. Pharmacokinetics, Fecal Output, and Grimace Scores in Rabbits Given Long-Acting Buprenorphine or Fentanyl for Postsurgical Analgesia. J Am Assoc Lab Anim Sci.; 2024.

20. New Zealand white rabbits receiving 0.15 mg/kg and 0.3 mg/kg SQ Ethiqa XR. Unpublished study 2021. Data on file.

21. Nair AB, Jacob S. A simple practice guide for dose conversion between animals and human. J Basic Clin Pharm. 7(2):27-31; 2016.

22. Food and Drug Administration. FDA Guidance for Industry Estimating the Maximum Safe Starting Dose in Initial Clinical Trials for Therapeutics in Adult Healthy Volunteers. July 2005.

MANUFACTURED FOR

Fidelis Animal Health, Inc.
685 US Highway One, Suite 265
North Brunswick, NJ 08902

833-384-4729
www.EthiqaXR.com

Fidelis, Fidelis Animal Health™, Ethiqa XR®, and Fidelipid LAI™ are trademarks of Fidelis Animal Health, Inc., a Delaware Corporation.

NDC 86084-100-30. U.S. Patent Nos. 10,555,899; 11,058,629

FID-ETH-PIR014

WARNING: Due to serious human safety and abuse concerns, read the entire package insert before using this drug, including the complete Boxed Warning.